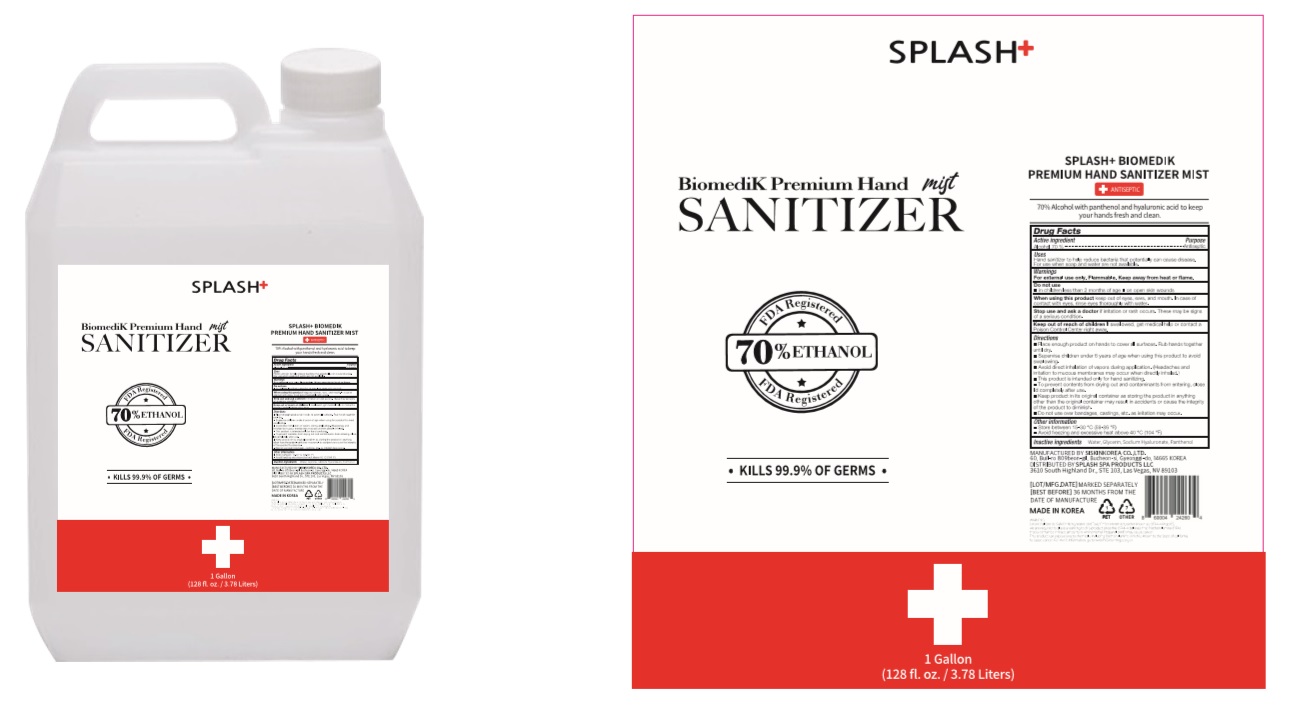 DRUG LABEL: BiomediK Premium Hand Sanitizer mist
NDC: 74514-1002 | Form: LIQUID
Manufacturer: SISKINKOREA CO.,LTD.
Category: otc | Type: HUMAN OTC DRUG LABEL
Date: 20200708

ACTIVE INGREDIENTS: ALCOHOL 2649.5 mL/3785 mL
INACTIVE INGREDIENTS: GLYCERIN; PANTHENOL; WATER; HYALURONATE SODIUM

BiomediK Premium Hand Sanitizer mist | Bottle+Cap+Pump | 74514-1002-1